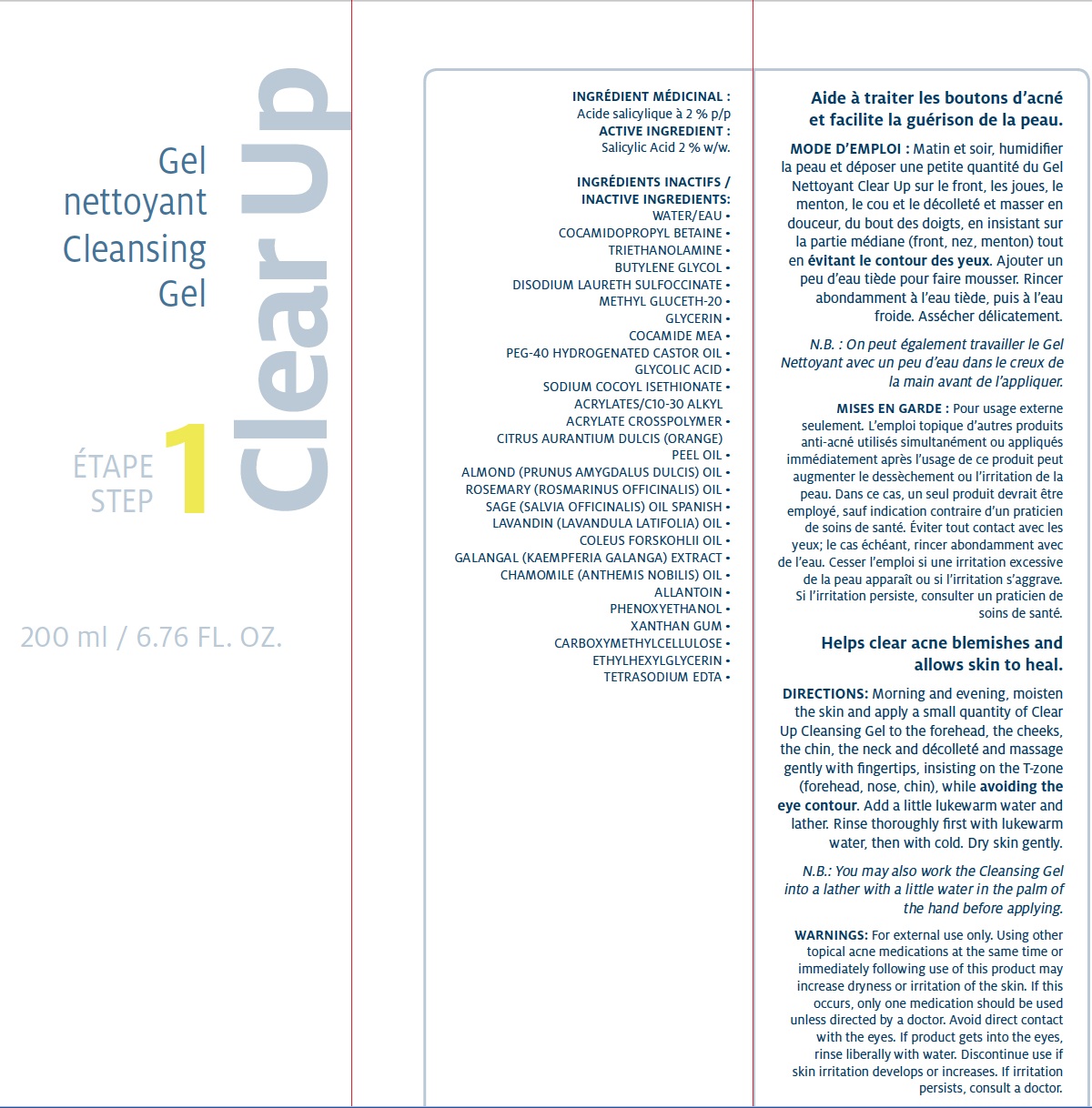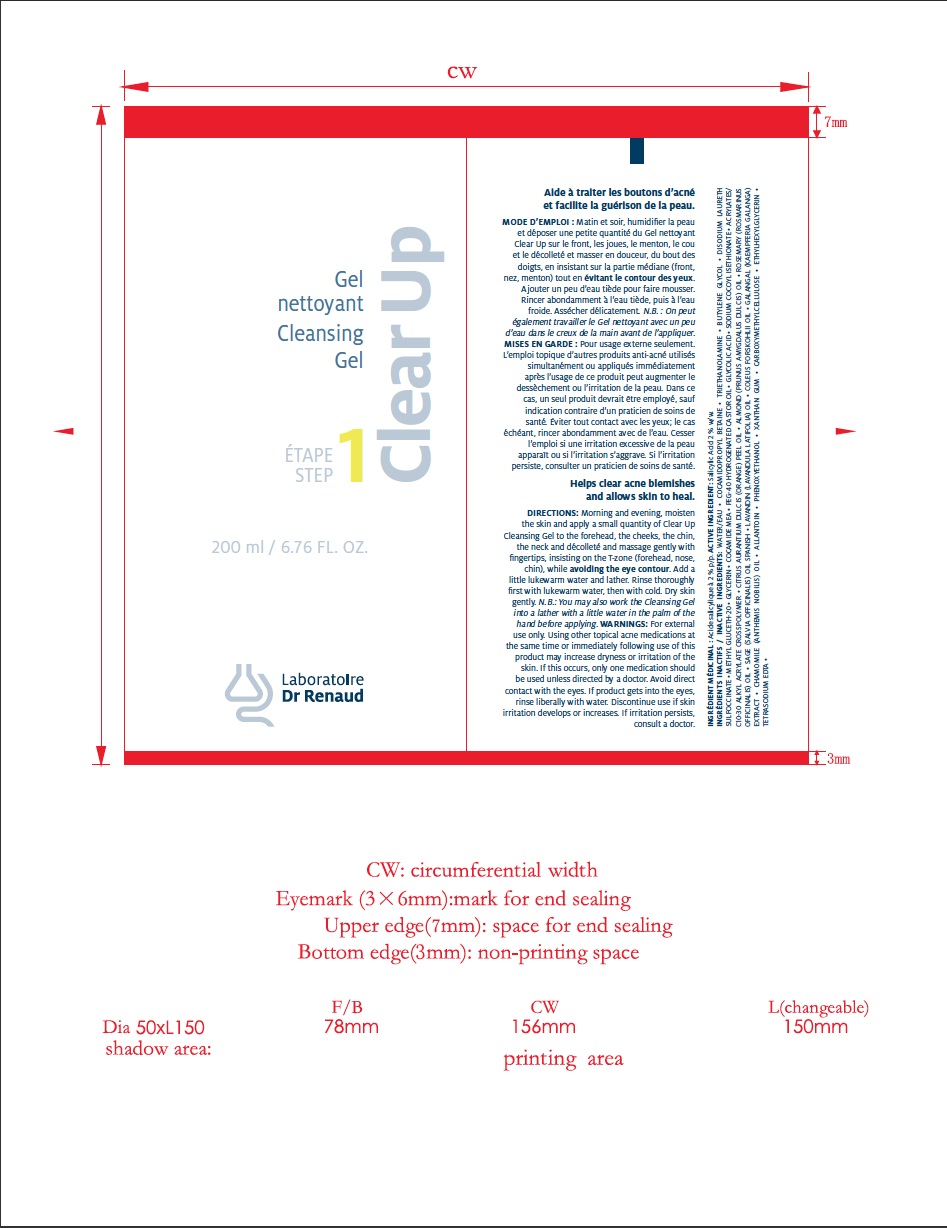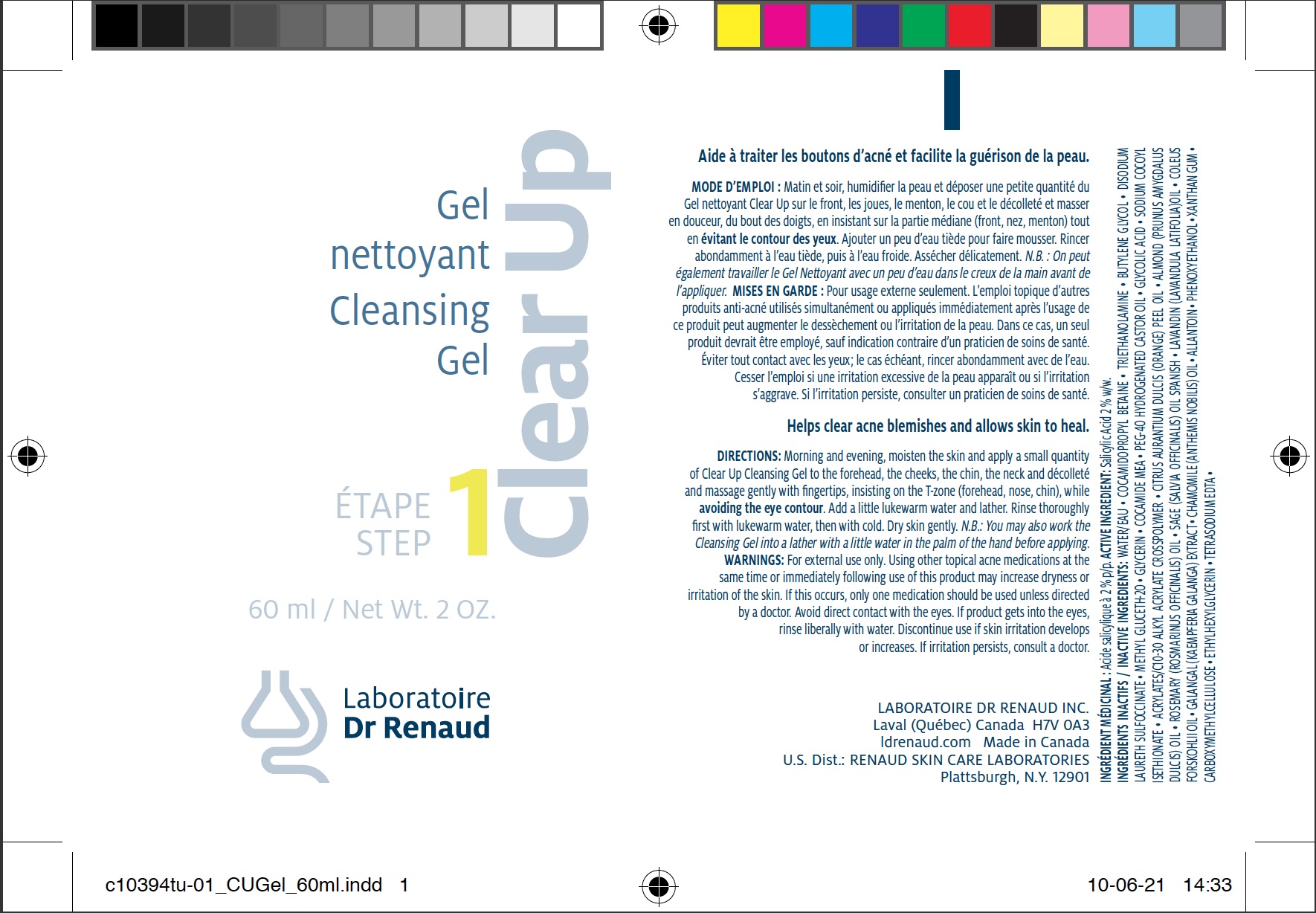 DRUG LABEL: CLEAR UP Cleansing
NDC: 62499-394 | Form: GEL
Manufacturer: Laboratoire Dr. Renaud
Category: otc | Type: HUMAN OTC DRUG LABEL
Date: 20100628

ACTIVE INGREDIENTS: SALICYLIC ACID 2 g/100 g
INACTIVE INGREDIENTS: WATER; COCAMIDOPROPYL BETAINE; TROLAMINE; BUTYLENE GLYCOL; DISODIUM LAURYL SULFOSUCCINATE; METHYL GLUCETH-20; GLYCERIN; POLYOXYL 40 HYDROGENATED CASTOR OIL; SODIUM GLYCOLATE; SODIUM COCOYL ISETHIONATE ; PHENOXYETHANOL; CARBOMER COPOLYMER TYPE A; ORANGE OIL; ALMOND OIL; SAGE OIL; LAVANDIN OIL; ETHYLHEXYLGLYCERIN; EDETATE SODIUM

Drug Facts

ACTIVE INGREDIENT

Salicylic Acid 2 % w/w

INACTIVE INGREDIENTS

WATER/EAU • COCAMIDOPROPYL BETAINE •
TRIETHANOLAMINE • BUTYLENE GLYCOL • DISODIUM LAURETH SULFOCCINATE •
METHYL GLUCETH-20 • GLYCERIN • COCAMIDE MEA • PEG-40 HYDROGENATED
CASTOR OIL • GLYCOLIC ACID • SODIUM COCOYL ISETHIONATE •
ACRYLATES/C10-30 ALKYL ACRYLATE CROSSPOLYMER • CITRUS AURANTIUM
DULCIS (ORANGE) PEEL OIL • ALMOND (PRUNUS AMYGDALUS DULCIS) OIL •
ROSEMARY (ROSMARINUS OFFICINALIS) OIL • SAGE (SALVIA OFFICINALIS)
OIL SPANISH • LAVANDIN (LAVANDULA LATIFOLIA)OIL • COLEUS FORSKOHLII OIL •
GALANGAL (KAEMPFERIA GALANGA) EXTRACT • CHAMOMILE (ANTHEMIS NOBILIS)
OIL • ALLANTOIN • PHENOXYETHANOL • XANTHAN GUM •
CARBOXYMETHYLCELLULOSE • ETHYLHEXYL GLYCERIN • TETRASODIUM EDTA

PURPOSE

For the treatment of acne. Helps clear acne blemishes and allows skin to heal.

DIRECTIONS

Morning and evening, moisten
the skin and apply a small quantity of CLEAR UP
Cleansing Gel to the forehead, the cheeks, the chin,
the neck and décolleté and massage gently with
fi ngertips, insisting on the T zone (forehead, nose,
chin), while avoiding the eye contour.
Add a little lukewarm water and lather.
Rinse thoroughly fi rst with lukewarm water,
then with cold. Dry skin gently.
N.B.: You may also work the Cleansing Gel
into a lather with a little water in the palm
of the hand before applying.

WARNINGS

For external use only. Using other
topical acne medications at the same time or
immediately following use of this product may
increase dryness or irritation of the skin. If this
occurs, only one medication should be used unless
directed by a doctor. Avoid direct contact with
the eyes. If product gets into the eyes, rinse
liberally with water. Discontinue use if skin
irritation develops or increases.
If irritation persists, consult a doctor.

image of carton 200ml label
image of tube 60 ml label
image of tube 200ml label

INDICATIONS AND USAGE

Enter section text here

Keep out of reach of children.